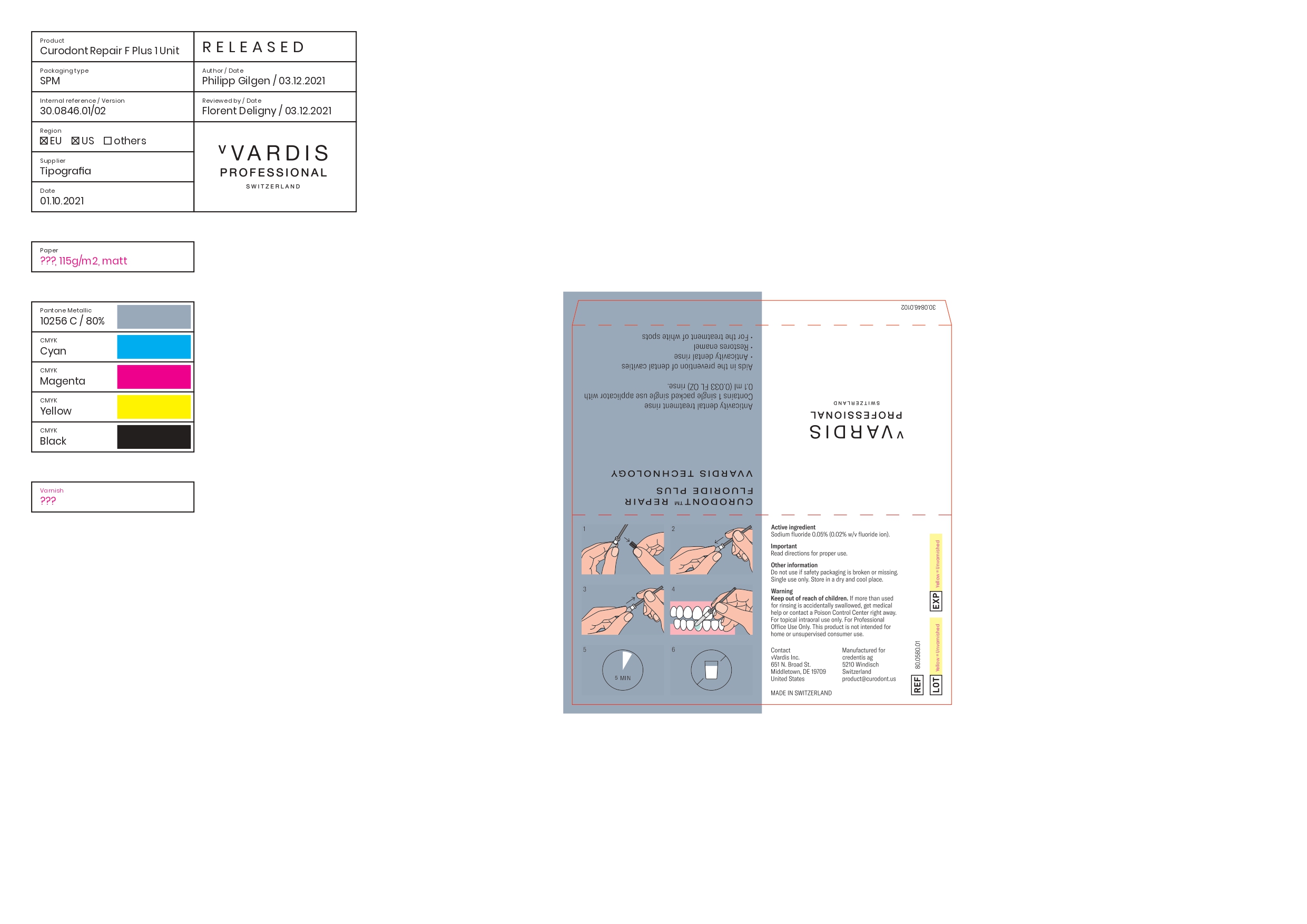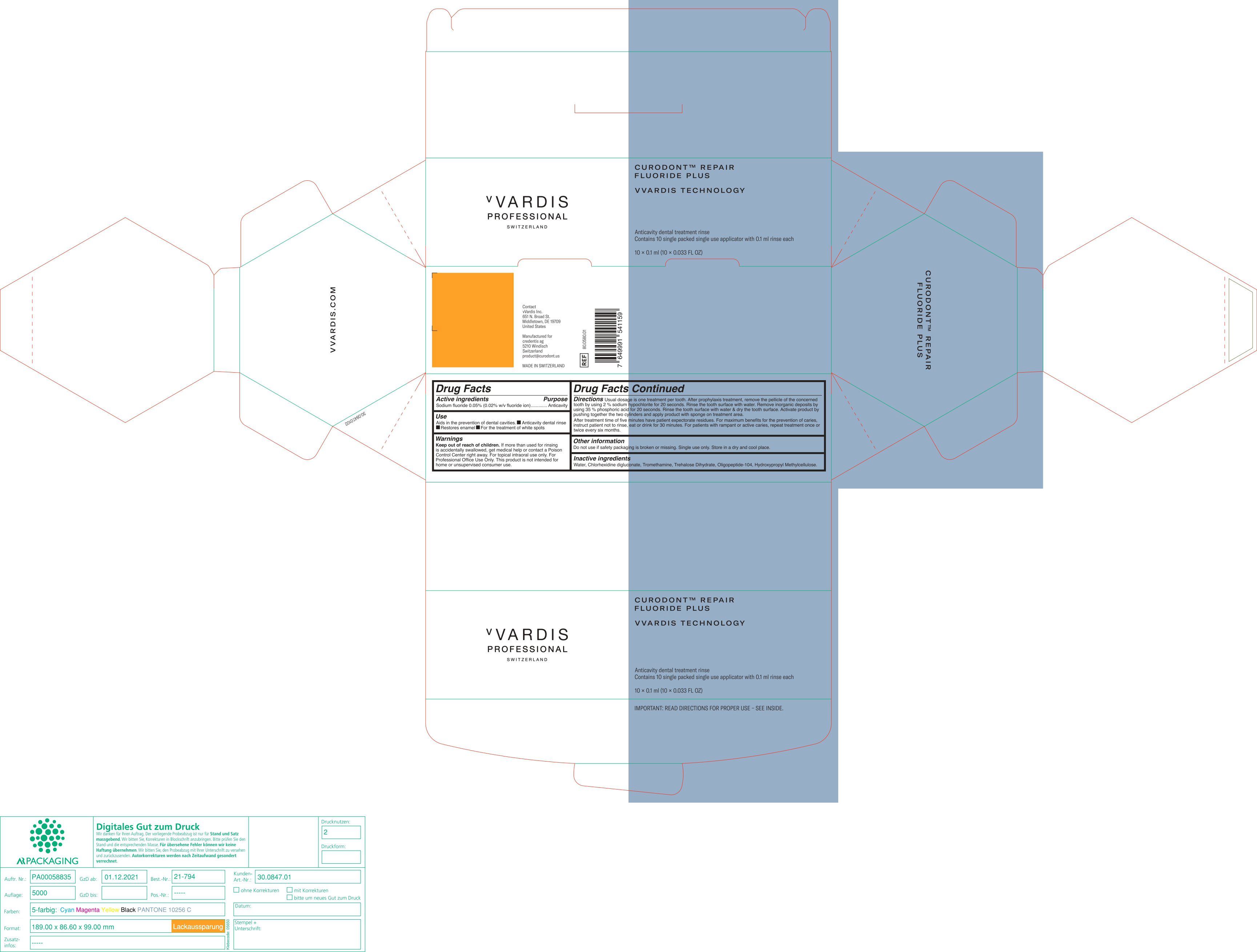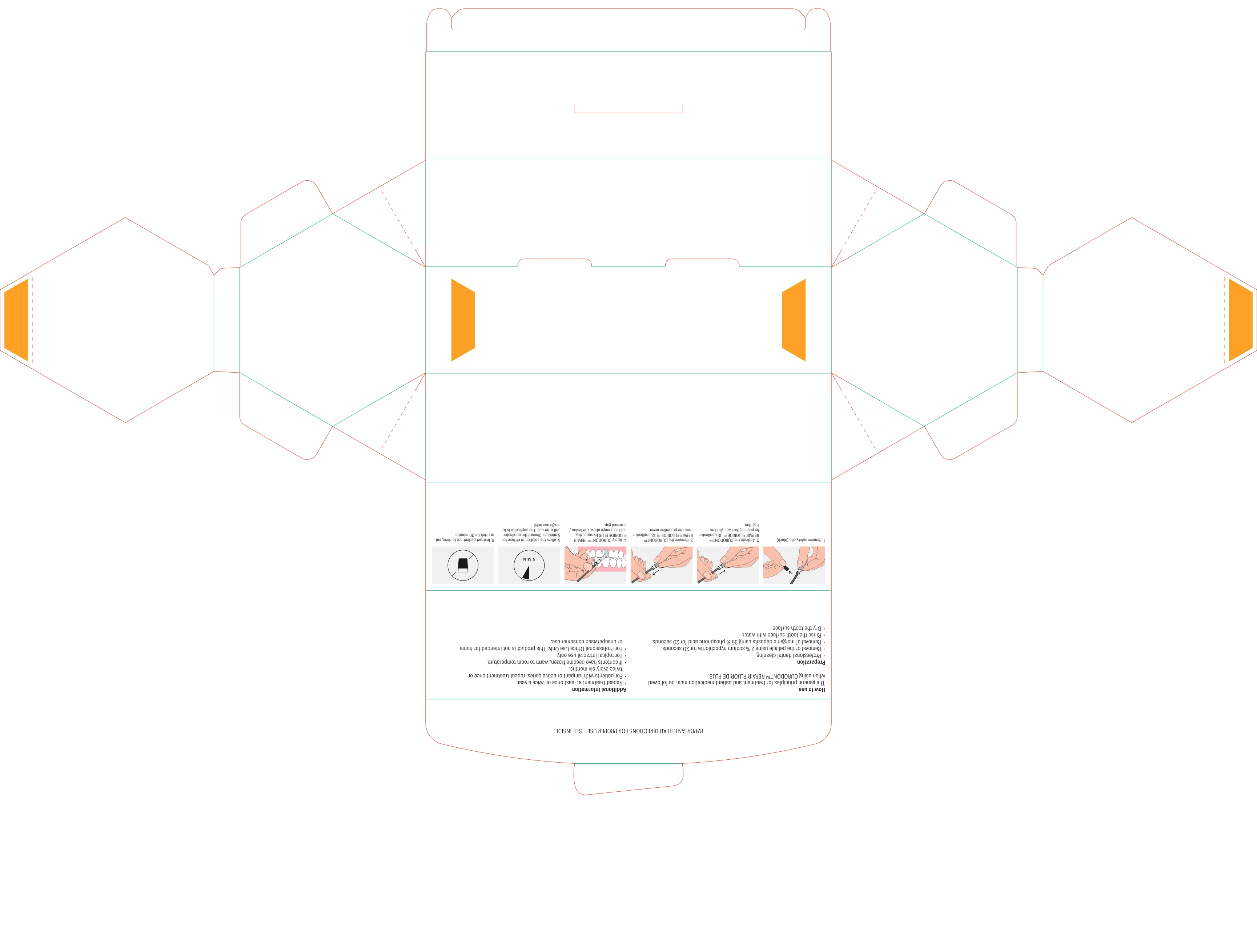 DRUG LABEL: CURODONT REPAIR FLUORIDE PLUS
NDC: 72247-101 | Form: SPONGE
Manufacturer: CREDENTIS AG
Category: otc | Type: HUMAN OTC DRUG LABEL
Date: 20220111

ACTIVE INGREDIENTS: SODIUM MONOFLUOROPHOSPHATE 0.02 g/100 mL
INACTIVE INGREDIENTS: WATER; CHLORHEXIDINE GLUCONATE; TROMETHAMINE; TREHALOSE DIHYDRATE; OLIGOPEPTIDE-10; HYPROMELLOSE, UNSPECIFIED

CREDENTIS - CURODONT REPAIR FLUORIDE PLUS - MAY CONSULTING

ACTIVE INGREDIENTS

SODIUM FLUORIDE 0.05% (0.02% W/V FLUORIDE ION)

PURPOSE

ANTICAVITY

USES

AIDS IN THE PREVENTION OF DENTAL CAVITIES

- ANTICAVITY DENTAL RINSE
- RESTORES ENAMEL
- FOR THE TREATMENT OF WHITE SPOTS

WARNING

FOR TOPICAL INTRAORAL USE ONLY. FOR PROFESSIONAL OFFICE USE ONLY. THIS PRODUCT IS NOT INTENDED FOR HOME OR UNSUPERVISED CONSUMER USE.

KEEP OUT OF REACH OF CHILDREN.

DIRECTIONS

Usual dosage is one treatment per tooth. After prophylaxis treatment, remove the pellicle of the concerned tooth by using 2% sodium hypochlorite for 10 seconds. rinse the tooth surface with water. Remove inorganic deposits by pushing together the two cylinders and apply product with sponge on treatment area.

After treatment time of five minutes have patient expectorate residues. For maximum benefits for the prevention of caries, instruct patient not to rinse, eat or drink for 30 minutes. For patients with rampant or active caries, repeat treatment once or twice every six months.

OTHER INFORMATION

DO NOT USE IF SAFETY PACHAGING IS BROKEN OR MISSING.

SINGLE USE ONLY.

STORE IN A DRY AND COOL PLACE.

INACTIVE INGREDIENTS

WATER, CHLORHEXIDINE DIGLUCONATE, TROMETHAMINE, TREHALOSE DIHYDRATE, OLIGOPEPTIDE-104, HYDROXYPROPYL METHYLCELLULOSE

PACKAGE LABEL

vVardis Professional Switzerland

Curodont (tm) Repair Fluoride Plus

vVardis technology

Anticavity dental treatment rinse

Contains 10 single packed single use applicator with 0.1ml rinse each

10 x 0.1 ml (10 x 0.033 FL OZ)

Important: read directions for proper use - see inside